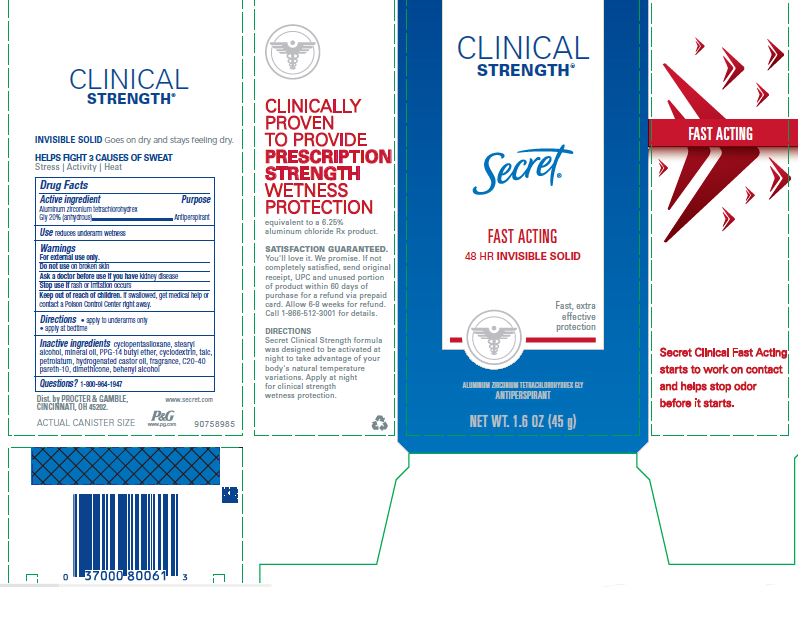 DRUG LABEL: Secret Clinical Strength Fast Acting Invisible
NDC: 69423-461 | Form: STICK
Manufacturer: The Procter & Gamble Manufacturing Company
Category: otc | Type: HUMAN OTC DRUG LABEL
Date: 20200416

ACTIVE INGREDIENTS: ALUMINUM ZIRCONIUM TETRACHLOROHYDREX GLY 20 g/100 g
INACTIVE INGREDIENTS: BETADEX; CYCLOMETHICONE 5; STEARYL ALCOHOL; MINERAL OIL; PPG-14 BUTYL ETHER; TALC; PETROLATUM; HYDROGENATED CASTOR OIL; C20-40 PARETH-10; DIMETHICONE; DOCOSANOL

Secret® Clinical Strength Fast Acting Invisible

Drug Facts

Active ingredient

Aluminum zirconium tetrachlorohydrex Gly 20% (anhydrous)

Purpose

Antiperspirant

Use

- reduces underarm wetness

Warnings

For external use only.

Do not use on broken skin

Ask a doctor before use if you have kidney disease

Stop use if rash or irritation occurs

Keep out of reach of children. If swallowed, get medical help or contact a Poison Control Center right away.

Directions

- apply to underarms only
- apply at bedtime

Inactive ingredients

cyclopentasiloxane, stearyl alcohol, mineral oil, PPG-14 butyl ether, cyclodextrin, talc, petrolatum, hydrogenated castor oil, fragrance, C20-40 pareth-10, dimethicone, behenyl alcohol

Questions?

1-800-964-1947

Dist. by PROCTER & GAMBLE,
CINCINNATI, OH 45202.

PRINCIPAL DISPLAY PANEL - 45 g Cylinder Carton

Secret®
CLINICAL
STRENGTH®

Fast Acting

48 HR Invisible Solid

ALUMINUM ZIRCONIUM TETRACHLOROHYDREX GLY
ANTIPERSPIRANT

NET WT. 1.6 OZ (45 g)